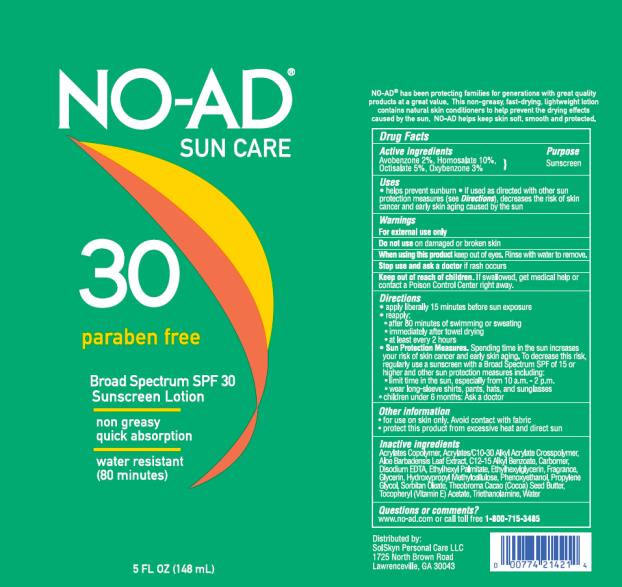 DRUG LABEL: NO-AD SPF30 5 OZ
NDC: 70281-111 | Form: LOTION
Manufacturer: SolSkyn Personal Care LLC
Category: otc | Type: HUMAN OTC DRUG LABEL
Date: 20180215

ACTIVE INGREDIENTS: AVOBENZONE 2 g/100 g; HOMOSALATE 10 g/100 g; OCTISALATE 5 g/100 g; OXYBENZONE 3 g/100 g
INACTIVE INGREDIENTS: WATER; CARBOMER INTERPOLYMER TYPE A (55000 CPS); ALOE VERA LEAF; CARBOXYPOLYMETHYLENE; WATERMELON; DIISOPROPYL ADIPATE; DISODIUM EDTA-COPPER; ETHYLHEXYLGLYCERIN; GLYCERIN; HYPROMELLOSES; PHENOXYETHANOL; SACCHARIDE ISOMERATE; SILICON DIOXIDE; SORBITAN MONOOLEATE; ALPHA-TOCOPHEROL ACETATE; TROLAMINE

NO-AD SPF30 LOTION 5OZ

NO-AD Sun Care Face Broad Spectrum SPF 30 Sunscreen Lotion

Active Ingredients

Avobenzone 2%, Homosalate 10%, Octisalate 5%, Oxybenzone 3%

Purpose

Sunscreen

Uses

- helps prevent sunburn
- if used as directed with other sun protection measures (see Directions), decreases the risk of skin cancer and early skin aging caused by the sun

Warnings

For external use only

Do not use

on damaged or broken skin

When using this product

keep out of eyes. Rinse with water to remove.

Stop use and ask a doctor

if rash occurs

Keep out of reach of children.

If swallowed, get medical help or contact a Poison Control Center right away.

Directions

- apply liberally 15 minutes before sun exposure
- reapply:
  • after 80 minutes of swimming or sweating
  • immediately after towel drying
  • at least every 2 hours
- Sun Protection Measures. Spending time in the sun increases your risk of skin cancer and early skin aging. To decrease this risk, regularly use a sunscreen with a Broad Spectrum SPF of 15 or higher and other sun protection measures including:
  • limit time in the sun, especially from 10 a.m. - 2 p.m.
  • wear long-sleeve shirts, pants, hats, and sunglasses
- children under 6 months: Ask a doctor

Other Information

- for use on skin only. Avoid contact with fabric
- protect this product from excessive heat and direct sun

Inactive Ingredients

Acrylates Copolymer, Acrylates/C10-30 Alkyl Acrylate Crosspolymer, Aloe Barbadensis Leaf Extract, Carbomer, Citrullus Vulgaris (Watermelon) Fruit Extract, Diisopropyl Adipate, Disodium EDTA, Ethylhexylglycerin, Glycerin, Hydroxypropyl Methylcellulose, Phenoxyethanol, Propanediol, Saccharide Isomerate, Silica, Sorbitan Oleate, Tocopheryl (Vitamin E) Acetate, Triethanolamine, Water

Questions or comments?

www.no-ad.com or call toll free 1-800-715-3485

PRINCIPAL DISPLAY PANEL

NO-AD
Suncare
30 Paraben free
SPF 30
5 FL OZ (148 mL)